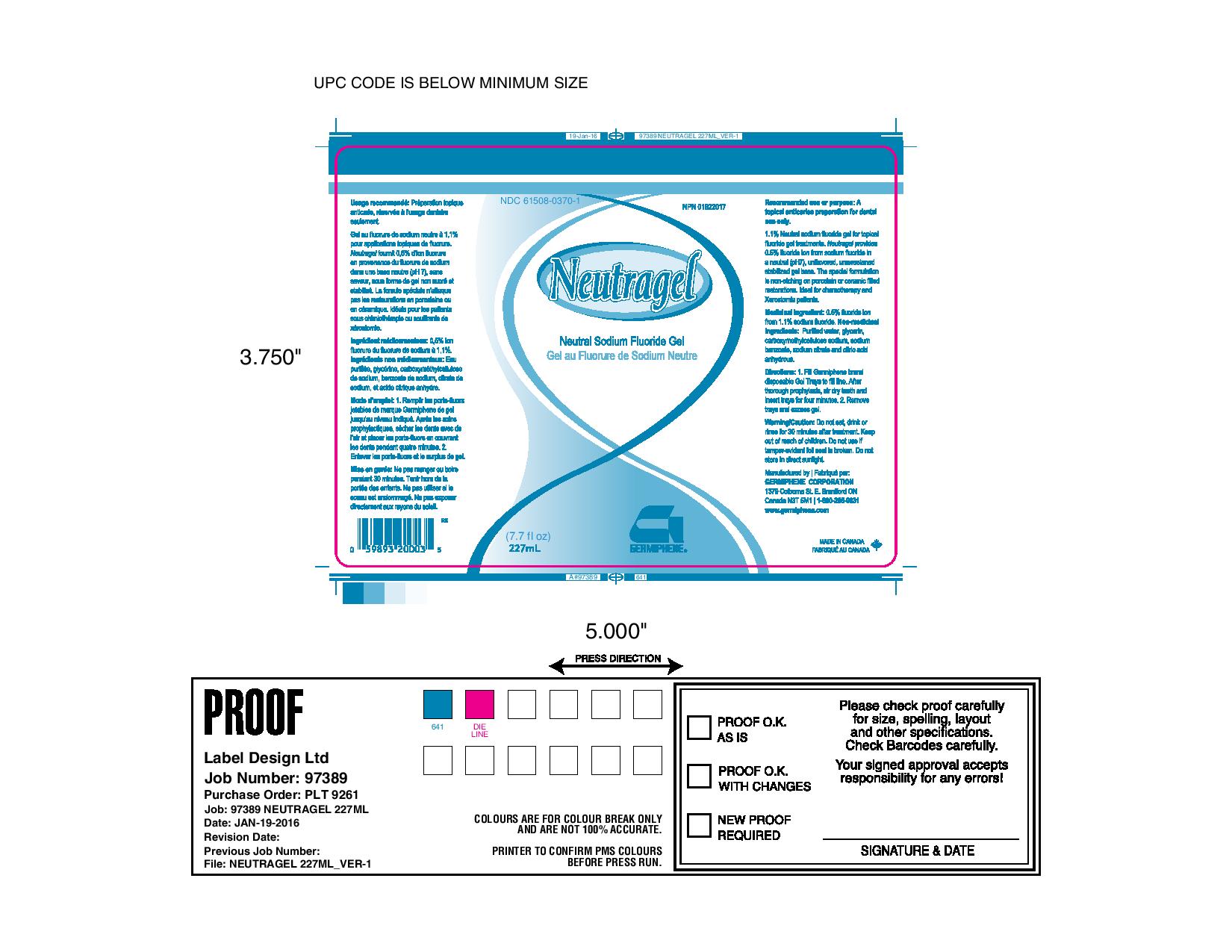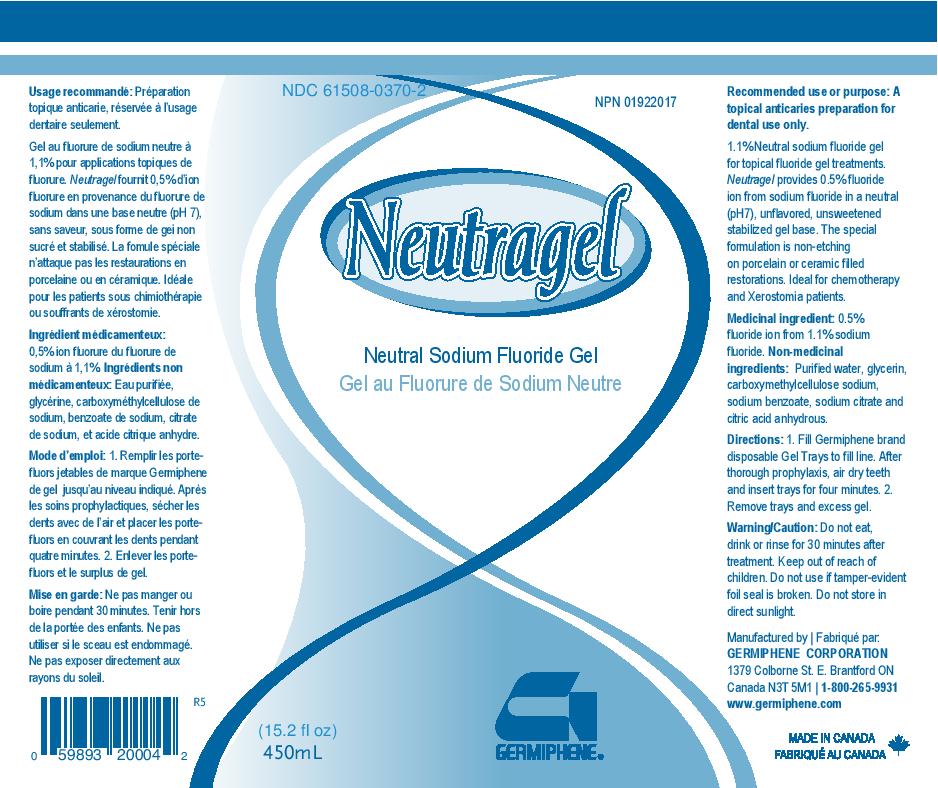 DRUG LABEL: Neutragel
NDC: 61508-0370 | Form: GEL, DENTIFRICE
Manufacturer: Germiphene Corporation
Category: otc | Type: HUMAN OTC DRUG LABEL
Date: 20170203

ACTIVE INGREDIENTS: SODIUM FLUORIDE 1.1 g/100 g
INACTIVE INGREDIENTS: CARBOXYMETHYLCELLULOSE SODIUM 2.6 g/100 g; WATER 86.1 g/100 g; GLYCERIN 10 g/100 g; SODIUM BENZOATE 0.12 g/100 g; ANHYDROUS CITRIC ACID 0.007 g/100 g; SODIUM CITRATE 0.093 g/100 g

Neutragel

Recommended use:

A topical anticaries preparation for dental use only.

PURPOSE

1.1% Neutral sodium fluoride gel for topical fluoride gel treatments. Neutragel provides 0.5% fluoride ion from sodium fluoride in a neutral (pH7), unflavored, unsweetened, stabilized gel base. The special formulation is non-etching on porcelain or ceramic filled restorations. Ideal for chemotherapy and Zerostomia patients.

Medicinal ingredient:

0.5% fluoride ion (from 1.1% sodium fluoride)

Non-medicinal ingredients:

Purified water, glycerin carboxymethylcellulose sodium, sodium benzoate, sodium citrate, and citric acid anhydrous.

Directions:

1. Fill Germiphene brand disposable Gel Trays. After thorough prophylaxis, air dry teeth and insert trays for four minutes. 2. Remove trays and excess gel.

Warning/Caution:

Do not eat, drink, or rinse for 30 minutes after treatment. Do not use if tamper-evident foil seal is broken. Do not store in direct sunlight.

Keep out of reach of children.